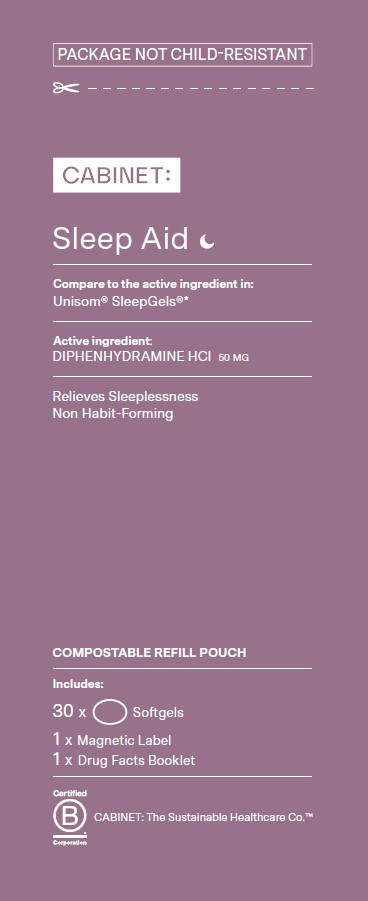 DRUG LABEL: Sleep Aid
NDC: 68210-4179 | Form: CAPSULE, LIQUID FILLED
Manufacturer: Spirit Pharmaceuticals LLC
Category: otc | Type: HUMAN OTC DRUG LABEL
Date: 20241211

ACTIVE INGREDIENTS: DIPHENHYDRAMINE HYDROCHLORIDE 50 mg/1 1
INACTIVE INGREDIENTS: FD&C BLUE NO. 1; GELATIN; GLYCERIN; POLYETHYLENE GLYCOL 400; PROPYLENE GLYCOL; SORBITOL; TITANIUM DIOXIDE; WATER

Sleep Aid

Active Ingredient (in each tablet)

Diphenhydramine HCI 50 mg

Purpose

Nighttime sleep-aid

Uses

• for relief of occasional sleeplessness

Do not use

• for children under 12 years of age • with any other product containing diphenhydramine, even one used on skin

Ask a doctor before use if you have

• a breathing problem such as emphysema or chronic bronchitis • glaucoma • trouble urinating due to an enlarged prostate gland

Ask a doctor or pharmacist before use if you are if you are

• taking sedatives or tranquilizers

When using this product

avoid alcoholic drinks

Stop use and ask a doctor if

sleeplessness persist continuously for more than 2 weeks. Insomnia may be a symptom of serious underlying medical illness.

If pregnant or breast-feeding,

ask a health professional before use.

Keep out of reach of children.

In case of overdose, get medical help or contact a Poison Control Center right away. (1-800-222-1222) Quick medical attention is critical for adults as well as for children even if you do not notice any signs or symptoms.

Directions

• adults and children 12 years of age and over: 1 softgel (50 mg) at bedtime if needed, or as directed by a doctor

Other information

• store between 20–25°C (68–77°F)

Inactive ingredients

FD&C Blue No. 1, gelatin, glycerin, polyethylene glycol 400, propylene glycol, sorbitol, titanium dioxide, water

Questions or comments?

1-888-333-9792

Distributed by:

Cabinet Health P.B.C.